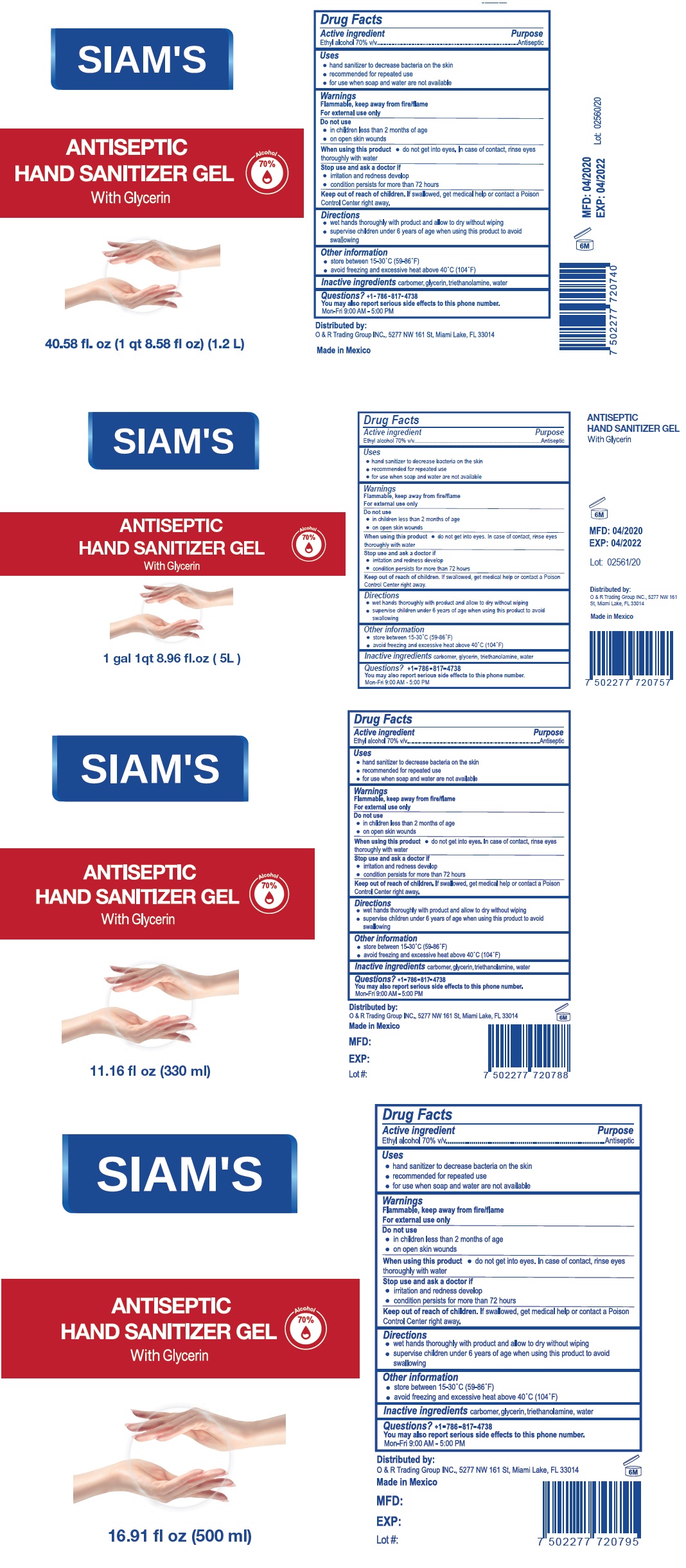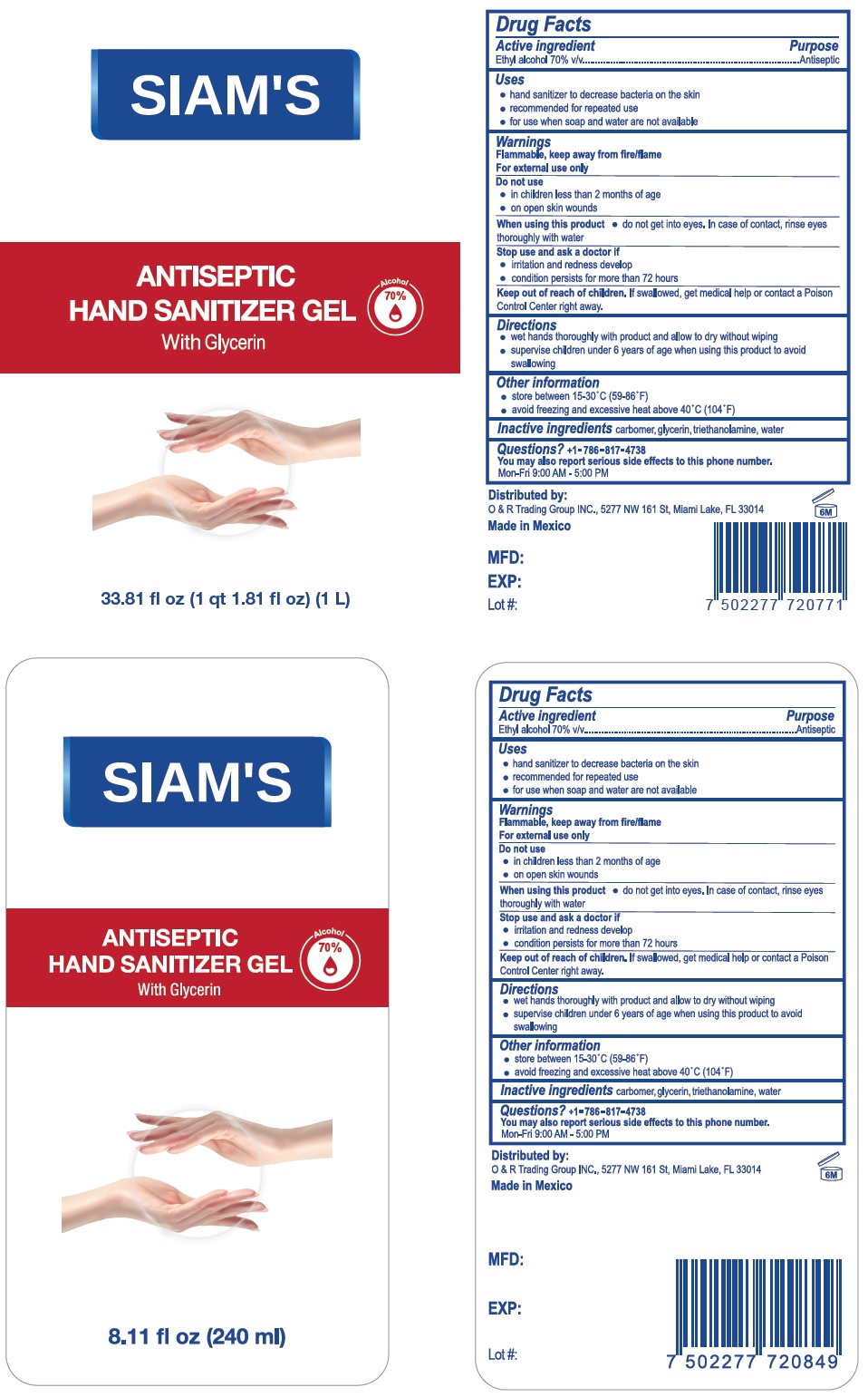 DRUG LABEL: SIAMS ANTISEPTIC HAND SANITIZER
NDC: 77420-001 | Form: GEL
Manufacturer: Creaciones Iguazú, S.A. de C.V.
Category: otc | Type: HUMAN OTC DRUG LABEL
Date: 20200521

ACTIVE INGREDIENTS: ALCOHOL 70 L/100 L
INACTIVE INGREDIENTS: CARBOMER HOMOPOLYMER, UNSPECIFIED TYPE; GLYCERIN; TROLAMINE; WATER

SIAM'S HAND SANITIZER

Active ingredient

Ethyl alcohol 70% v/v

Purpose

Antiseptic

Uses

- hand sanitizer to decrease bacteria on the skin
- recommended for repeated use
- for use when soap and water are not available

Warnings

Flammable, keep away from fire/flame

For external use only

Do not use

- in children less than 2 months of age
- on open skin wounds

When using this product • do not get into eyes. In case of contact, rinse eyes thoroughly with water

Stop use and ask a doctor if

- irritation and redness develop
- condition persists for more than 72 hours

Keep out of reach of children. If swallowed, get medical help or contact a Poison Control Center right away.

Directions

- wet hands thoroughly with product and allow to dry without wiping
- supervise children under 6 years of age when using this product to avoid swallowing

Other information

- store between 15-30^0C (59-86^0F)
- avoid freezing and excessive heat above 40^0C (104^0F)

Inactive ingredients carbomer, glycerin, triethanolamine, water

Questions? +1-786-817-4738

You may also report serious side effects to this phone number.

Mon-Fri 9:00 AM-5:00 PM

With Glycerin

Distributed by:

O & R Trading Group INC., 5277 NW 161 St, Miami Lake, FL 33014

Made in Mexico